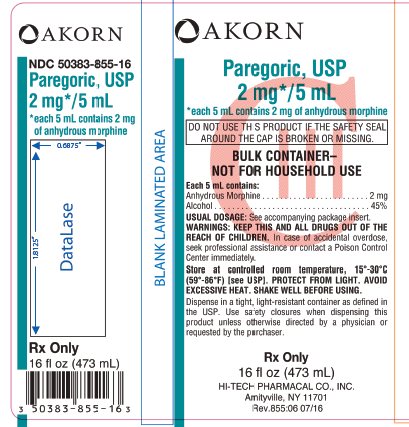 DRUG LABEL: Paregoric
NDC: 50383-855 | Form: LIQUID
Manufacturer: Hi-Tech Pharmacal Co., Inc.
Category: prescription | Type: HUMAN PRESCRIPTION DRUG LABEL
Date: 20181203
DEA Schedule: CIII

ACTIVE INGREDIENTS: MORPHINE 2 mg/5 mL
INACTIVE INGREDIENTS: ALCOHOL; ANISE OIL; BENZOIC ACID; WATER; GLYCERIN; CAMPHOR OIL

Paregoric, USP

*each 5 mL contains 2 mg of anhydrous morphine

Rx Only

DESCRIPTION

Each 5 mL contains:

Anhydrous Morphine .......................................................................................................... 2 mg

(from opium tincture)

Alcohol ................................................................................................................................ 45%

Inactive Ingredients: anise oil, benzoic acid, camphor, alcohol, glycerin, and purified water.

CLINICAL PHARMACOLOGY

Morphine produces its major effects on the central nervous system (CNS) and on the bowel.

INDICATIONS AND USAGE

Paregoric is useful for the treatment of diarrhea.

CONTRAINDICATIONS

Hypersensitivity to morphine. Because of its stimulating effect on the spinal cord, morphine should not be used in convulsive states, such as those occurring in status epilepticus, tetanus, and strychnine poisoning.

This preparation should not be used in diarrhea caused by poisoning until the toxic material is eliminated from the gastrointestinal tract.

PRECAUTIONS

General

Head Injury and Increased Intracranial Pressure - The respiratory depressant effects of narcotics and their capacity to elevate cerebrospinal-fluid pressure may be markedly exaggerated in the presence of head injury, other intracranial lesions, or a preexisting increase in intracranial pressure. Furthermore, narcotics produce additional effects that may obscure the clinical course in patients with head injuries.

Acute Abdominal Conditions - The administration of morphine or other narcotics may obscure the diagnosis or clinical course in patients with acute abdominal conditions.

Special-Risk Patients - Morphine should be given with caution to certain patients, such as the elderly or debilitated and those with severe impairment of hepatic or renal function, hypothyroidism, Addison’s disease, and prostatic hypertrophy or urethral stricture.

Morphine should be used with extreme caution in patients with disorders characterized by hypoxia, since even usual therapeutic doses of narcotics may decrease respiratory drive to the point of apnea while simultaneously increasing airway resistance.

Hypotensive Effect - The administration of morphine may result in severe hypotension in the postoperative patient or any individual whose ability to maintain blood pressure has been compromised by a depleted blood volume or the administration of such drugs as the phenothiazines or certain anesthetics.

Supraventricular Tachycardias - Because of a possible vagolytic action that may produce a significant increase in the ventricular response rate, morphine should be used with caution in patients with atrial flutter and other supraventricular tachycardias.

Convulsions - Morphine may aggravate preexisting convulsions in patients with convulsive disorders. If dosage is escalated substantially above recommended levels because of tolerance development, convulsions may occur in individuals without a history of convulsive disorders.

Information for Patients

Morphine may impair the mental and/or physical abilities required for the performance of potentially hazardous tasks, such as driving a car or operating machinery.

Interactions

Drug Interactions

Morphine in combination with other narcotic analgesics, general anesthetics, phenothiazines, tranquilizers, sedative/hypnotics, or other CNS depressants (including alcohol) has additive depressant effects, and the patient should be so advised. When such combination therapy is contemplated, the dosage of one or both agents should be reduced.

Carcinogenesis, Mutagenesis, Impairment of Fertility

Paregoric has no known carcinogenic or mutagenic potential. However, no long-term animal studies are available to support this observation.

Usage in Pregnancy

Pregnancy Category C – Animal reproduction studies have not been conducted with morphine. It is not known whether morphine can cause fetal harm when administered to a pregnant woman or can affect reproduction capacity. Paregoric should be given to a pregnant woman only if clearly needed.

Nursing Mothers

Morphine appears in the milk of nursing mothers. Caution should be exercised when paregoric is administered to a nursing woman.

ADVERSE REACTIONS

The most frequent adverse reactions include lightheadedness, dizziness, sedation, nausea, and vomiting. These effects seem to be more prominent in ambulatory than in nonambulatory patients, and some of these adverse reactions may be alleviated if the patient lies down.

Other adverse reactions include euphoria, dysphoria, constipation, and pruritus.

To report SUSPECTED ADVERSE REACTIONS, contact Hi-Tech Pharmacal Co., Inc. at 1- 800-262-9010 or FDA at 1-800-FDA-1088 or www.fda.gov/medwatch.

DRUG ABUSE AND DEPENDENCE

Controlled Substance

Paregoric is a Schedule lll narcotic.

Dependence

Morphine can produce drug dependence and, therefore, has the potential for being abused. Patients receiving therapeutic dosage regimens of 10 mg every 4 hours for 1 to 2 weeks have exhibited mild withdrawal symptoms. Development of the dependent state is recognizable by an increased tolerance to the analgesic effect and the appearance of purposive phenomena (complaints, pleas, demands, or manipulative actions) shortly before the time of the next scheduled dose. A patient in withdrawal should be treated in a hospital environment. Usually, it is necessary only to provide supportive care with administration of a tranquilizer to suppress anxiety. Severe symptoms of withdrawal may require administration of a replacement narcotic.

OVERDOSAGE

Signs and Symptoms

Serious overdosage of morphine is characterized by respiratory depression (a decrease in respiratory rate and/or tidal volume, Cheyne-Stokes respiration, cyanosis), extreme somnolence progressing to stupor or coma, skeletal muscle flaccidity, cold and clammy skin, and, sometimes, bradycardia and hypotension. In severe overdosage, apnea, circulatory collapse, cardiac arrest, and death may occur.

Treatment

Primary attention should be given to the reestablishment of adequate respiratory exchange through provision of a patent airway and institution of assisted or controlled ventilation. The narcotic antagonist naloxone hydrochloride is a specific antidote against the respiratory depression that may result from overdosage or unusual sensitivity to narcotics. Therefore, an appropriate dose of the antagonist should be administered, preferably by the intravenous route, simultaneously with efforts at respiratory resuscitation. Since the duration of action of morphine may exceed that of the antagonist, the patient should be kept under continued surveillance, and repeated doses of the antagonist should be administered as needed to maintain adequate respiration.

Oxygen, intravenous fluids, vasopressors, and other supportive measures should be employed as indicated.

DOSAGE AND ADMINISTRATION

Usual Pediatric Dosage

0.25 to 0.5 mL/kg of body weight 1 to 4 times a day or as directed by a physician.

Usual Adult Dosage

5 to 10 mL 1 to 4 times a day or as directed by a physician.

HOW SUPPLIED

Paregoric, USP 2 mg*/5 mL, *each 5 mL contains 2 mg of anhydrous morphine (from opium tincture); alcohol 45% and is available in 16 fl. oz (473 mL) bottles.

RECOMMENDED STORAGE

Store at controlled room temperature, 15°-30°C (59°-86°F) [see USP].

PROTECT FROM LIGHT

AVOID EXCESSIVE HEAT

SHAKE WELL BEFORE USING

NOTE: This product may deposit a sediment if exposed to low temperatures. Filter if necessary.

Dispense in a tight, light-resistant container as defined in the USP. Use safety closures when dispensing this product unless otherwise directed by a physician or requested by the purchaser.

Rx Only

Manufactured By:

HI-TECH PHARMACAL CO., INC.

Amityville, NY 11701

Rev. 855:05 03/16

Package/Label Display Panel

Paregoric, USP

2 mg*/5 mL

*each 5 mL contains 2 mg of anhydrous morphine

DO NOT USE THIS PRODUCT IF THE SAFETY SEAL AROUND THE CAP IS BROKEN OR MISSING.

BULK CONTAINER-

NOT FOR HOUSEHOLD USE

Each 5 mL contains:

Anhydrous Morphine ………………………….2 mg

Alcohol ………………………………………...45%

USUAL USAGE: See accompanying package insert.

WARNING: KEEP THIS AND ALL DRUGS OUT OF REACH OF CHILDREN. In case of accidental overdose, seek professional assistance or contact a Poison Control Center immediately.

Store at controlled room temperature, 15° - 30°C (59°-86°F) [see USP]. PROTECT FROM LIGHT. AVOID EXCESSIVE HEAT. SHAKE WELL BEFORE USING.

Dispense in a tight, light-resistant container as defined in the USP. Use safety closures when dispensing this product unless otherwise directed by a physician or requested by the purchaser.

Rx Only

16 fl oz (473 mL)

HI-TECH PHARMACAL CO., INC.

Amityville, NY 11701

Rev.855:06 07/16